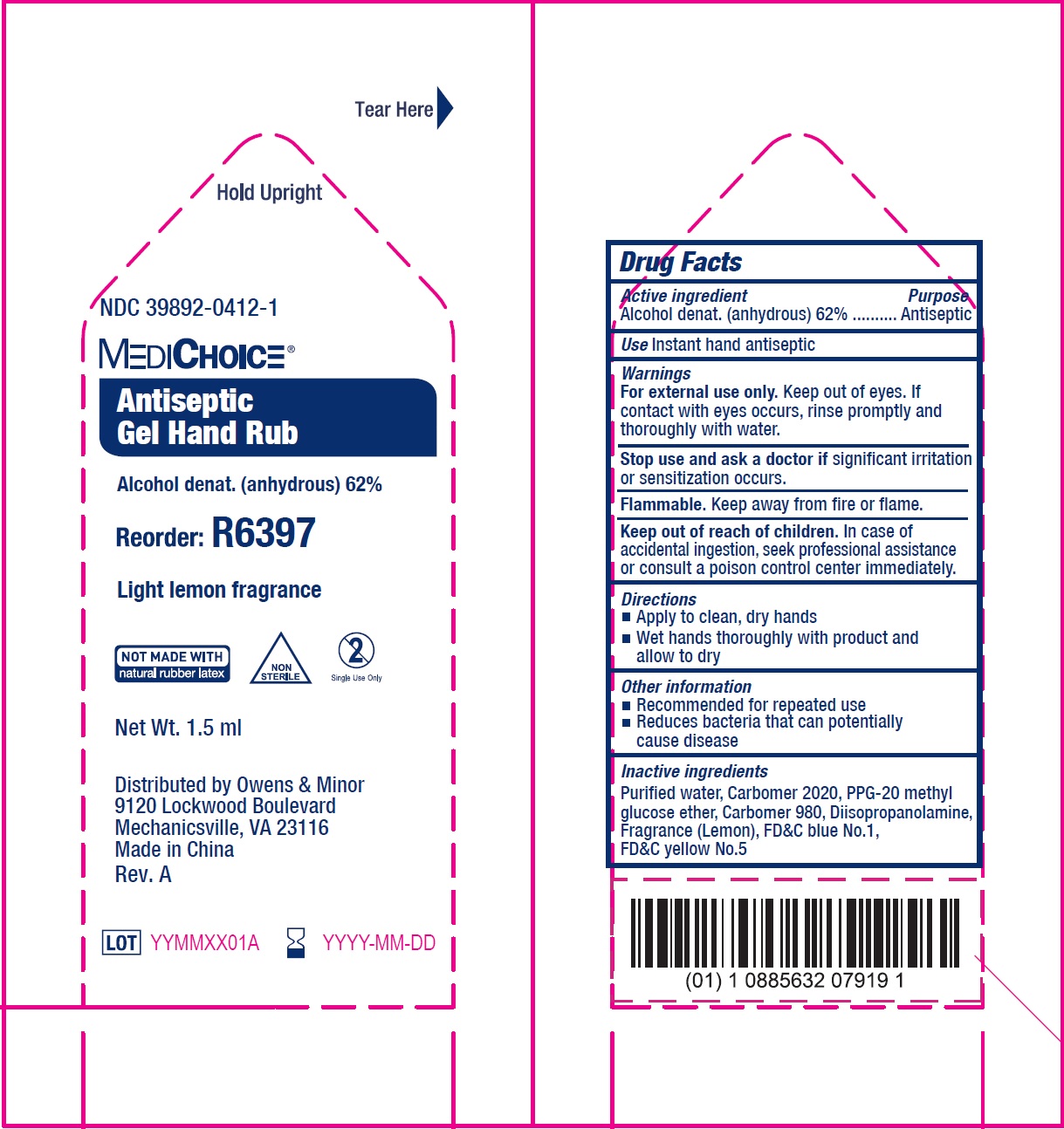 DRUG LABEL: Antiseptic Hand Rub
NDC: 39892-0412 | Form: GEL
Manufacturer: O&M HALYARD, INC.
Category: otc | Type: HUMAN OTC DRUG LABEL
Date: 20251008

ACTIVE INGREDIENTS: ALCOHOL 620 mg/1 mL
INACTIVE INGREDIENTS: WATER; PPG-20 METHYL GLUCOSE ETHER; DIISOPROPANOLAMINE; LEMON; FD&C BLUE NO. 1; FD&C YELLOW NO. 5

Antiseptic Gel Hand Rub

Active ingredient

Alcohol denat. (anhydrous) 62%

Purpose

Antiseptic

Use

Instant hand antiseptic

Warnings

Keep out of eyes. If contact with eyes occurs, rinse promptly and thoroughly with water. For external use only.

Keep away from fire or flame. Flammable.

Stop use and ask a doctor

if significant irritation or sensitization occurs.

Keep out of reach of children.

In case of accidental ingestion, seek professional assistance or consult a poison control center immediately.

Directions

- Apply to clean, dry hands
- Wet hands thoroughly with product and allow to dry

Other information

- Recommended for repeated use
- Reduces bacteria that can potentially cause disease

Inactive ingredients

Purified water, Carbomer 2020, PPG-20 methyl glucose ether, Carbomer 980, Diisopropanolamine, Fragrance (Lemon), FD&C blue No.1, FD&C yellow No.5